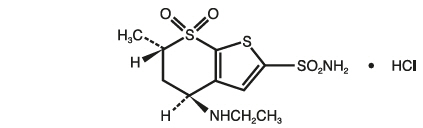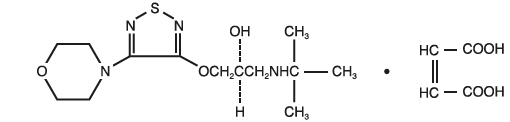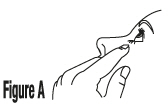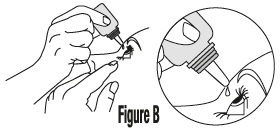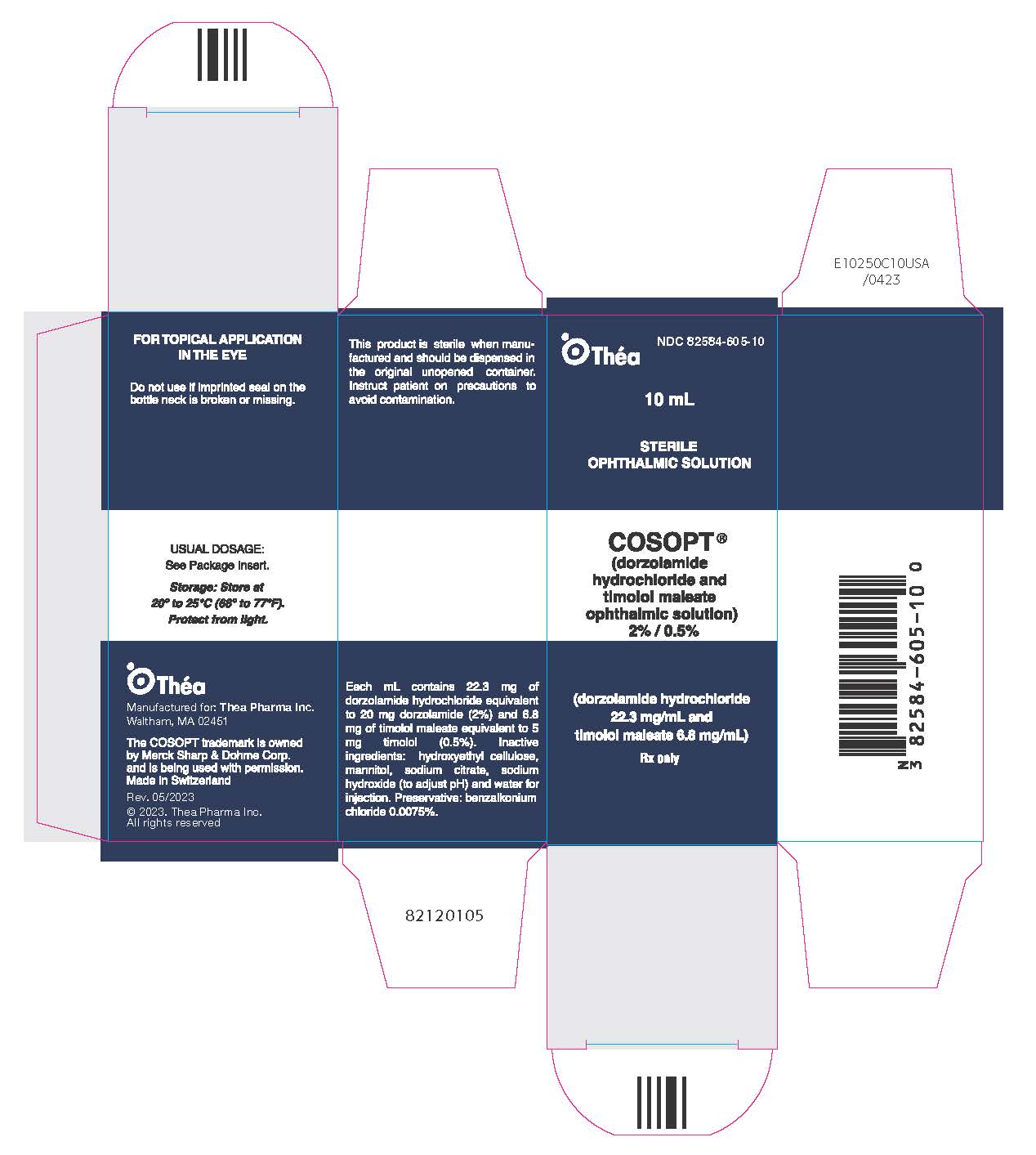 DRUG LABEL: COSOPT
NDC: 82584-605 | Form: SOLUTION/ DROPS
Manufacturer: Thea Pharma Inc.
Category: prescription | Type: HUMAN PRESCRIPTION DRUG LABEL
Date: 20240417

ACTIVE INGREDIENTS: DORZOLAMIDE HYDROCHLORIDE 20 mg/1 mL; TIMOLOL MALEATE 5 mg/1 mL
INACTIVE INGREDIENTS: HYDROXYETHYL CELLULOSE (2000 MPA.S AT 1%); MANNITOL; SODIUM CITRATE, UNSPECIFIED FORM; SODIUM HYDROXIDE; WATER; BENZALKONIUM CHLORIDE

HIGHLIGHTS OF PRESCRIBING INFORMATION

These highlights do not include all the information needed to use COSOPT safely and effectively. See full prescribing information for COSOPT.
COSOPT® (dorzolamide hydrochloride and timolol maleate ophthalmic solution), for topical ophthalmic use
Initial U.S. Approval: 1998

1 INDICATIONS AND USAGE

- COSOPT is a combination of dorzolamide hydrochloride, a carbonic anhydrase inhibitor, and timolol maleate, a beta-adrenergic receptor blocking agent, indicated for the reduction of elevated intraocular pressure (IOP) in patients with open-angle glaucoma or ocular hypertension who are insufficiently responsive to beta-blockers.
- The IOP-lowering of COSOPT twice daily was slightly less than that seen with the concomitant administration of 0.5% timolol twice daily, and 2% dorzolamide three times daily. (1)

2 DOSAGE AND ADMINISTRATION

The dose is one drop of COSOPT in the affected eye(s) two times daily. (2)

3 DOSAGE FORMS AND STRENGTHS

Ophthalmic solution containing dorzolamide 20 mg/mL (2%) and timolol 5 mg/mL (0.5%). (3)

4 CONTRAINDICATIONS

COSOPT is contraindicated in patients with:

- Bronchial asthma or a history of bronchial asthma, severe chronic obstructive pulmonary disease. (4.1)
- Sinus bradycardia, second or third degree atrioventricular block, overt cardiac failure, cardiogenic shock. (4.2)
- Hypersensitivity to any component of this product. (4.3, 5.3)

5 WARNINGS AND PRECAUTIONS

- Potentiation of Respiratory Reactions Including Asthma (5.1)
- Cardiac Failure (5.2)
- Sulfonamide Hypersensitivity (5.3)
- Obstructive Pulmonary Disease (5.4)
- Increased Reactivity to Allergens (5.5)
- Potentiation of Muscle Weakness (5.6)
- Masking of Hypoglycemic Symptoms in Patients with Diabetes Mellitus (5.7)
- Masking of Thyrotoxicosis (5.8)
- Renal and Hepatic Impairment (5.9)
- Impairment of Beta-Adrenergically Mediated Reflexes During Surgery (5.10)

6 ADVERSE REACTIONS

The most frequently reported adverse reactions were taste perversion (bitter, sour, or unusual taste) or ocular burning and/or stinging in up to 30% of patients. Conjunctival hyperemia, blurred vision, superficial punctate keratitis or eye itching were reported between 5 to 15% of patients. (6)

To report SUSPECTED ADVERSE REACTIONS, contact Thea Pharma Inc., at 1-833-838-4028 or FDA at 1-800-FDA-1088 or www.fda.gov/medwatch.

7 DRUG INTERACTIONS

- Potential additive effect of oral carbonic anhydrase inhibitor with COSOPT. (7.1)
- Potential acid-base and electrolyte disturbances. (7.2)
- Concomitant use with systemic beta-blockers may potentiate systemic beta-blockade. (7.3)
- Oral or intravenous calcium antagonists may cause atrioventricular conduction disturbances, left ventricular failure, and hypotension. (7.4)
- Catecholamine-depleting drugs may have additive effects and produce hypotension and/or marked bradycardia. (7.5)
- Digitalis and calcium antagonists, may have additive effects in prolonging atrioventricular conduction time. (7.6)
- CYP2D6 inhibitors may potentiate systemic beta-blockade. (7.7)

FULL PRESCRIBING INFORMATION

1 INDICATIONS AND USAGE

COSOPT® is indicated for the reduction of elevated intraocular pressure (IOP) in patients with open-angle glaucoma or ocular hypertension who are insufficiently responsive to beta-blockers (failed to achieve target IOP determined after multiple measurements over time). The IOP-lowering of COSOPT administered twice a day was slightly less than that seen with the concomitant administration of 0.5% timolol administered twice a day and 2% dorzolamide administered three times a day [see Clinical Studies (14)] .

2 DOSAGE AND ADMINISTRATION

The dose is one drop of COSOPT in the affected eye(s) two times daily.

If more than one topical ophthalmic drug is being used, the drugs should be administered at least five minutes apart [see Drug Interactions (7.3)] .

3 DOSAGE FORMS AND STRENGTHS

Ophthalmic solution containing dorzolamide 20 mg/mL (2%) equivalent to 22.26 mg/mL of dorzolamide hydrochloride, and timolol 5 mg/mL (0.5%) equivalent to 6.83 mg/mL of timolol maleate.

4 CONTRAINDICATIONS

4.1 Asthma, COPD

COSOPT is contraindicated in patients with bronchial asthma, a history of bronchial asthma, or severe chronic obstructive pulmonary disease [see Warnings and Precautions (5.1)] .

4.2 Sinus Bradycardia, AV Block, Cardiac Failure, Cardiogenic Shock

COSOPT is contraindicated in patients with sinus bradycardia, second or third degree atrioventricular block, overt cardiac failure, and cardiogenic shock [see Warnings and Precautions (5.2)] .

4.3 Hypersensitivity

COSOPT is contraindicated in patients who are hypersensitive to any component of this product [see Warnings and Precautions (5.3)] .

5 WARNINGS AND PRECAUTIONS

5.1 Potentiation of Respiratory Reactions Including Asthma

COSOPT contains timolol maleate, a beta-adrenergic blocking agent; and although administered topically, is absorbed systemically. Therefore, the same types of adverse reactions that are attributable to systemic administration of beta-adrenergic blocking agents may occur with topical administration. For example, severe respiratory reactions, including death due to bronchospasm in patients with asthma, and rarely death in association with cardiac failure, have been reported following systemic or ophthalmic administration of timolol maleate [see Contraindications (4.1)] .

5.2 Cardiac Failure

Sympathetic stimulation may be essential for support of the circulation in individuals with diminished myocardial contractility, and its inhibition by beta-adrenergic receptor blockade may precipitate more severe failure.

In patients without a history of cardiac failure continued depression of the myocardium with beta-blocking agents over a period of time can, in some cases, lead to cardiac failure. At the first sign or symptom of cardiac failure, COSOPT should be discontinued [see Contraindications (4.2)] .

5.3 Sulfonamide Hypersensitivity

COSOPT contains dorzolamide, a sulfonamide; and although administered topically, it is absorbed systemically. Therefore, the same types of adverse reactions that are attributable to sulfonamides may occur with topical administration of COSOPT. Fatalities have occurred, although rarely, due to severe reactions to sulfonamides including Stevens-Johnson syndrome, toxic epidermal necrolysis, fulminant hepatic necrosis, agranulocytosis, aplastic anemia, and other blood dyscrasias. Sensitization may recur when a sulfonamide is readministered irrespective of the route of administration. If signs of serious reactions or hypersensitivity occur, discontinue the use of this preparation [see Contraindications (4.3)] .

5.4 Obstructive Pulmonary Disease

Patients with chronic obstructive pulmonary disease (e.g., chronic bronchitis, emphysema) of mild or moderate severity, bronchospastic disease, or a history of bronchospastic disease (other than bronchial asthma or a history of bronchial asthma, in which COSOPT is contraindicated) should, in general, not receive beta-blocking agents, including COSOPT [see Contraindications (4.1)] .

5.5 Increased Reactivity to Allergens

While taking beta-blockers, patients with a history of atopy or a history of severe anaphylactic reactions to a variety of allergens may be more reactive to repeated accidental, diagnostic, or therapeutic challenge with such allergens. Such patients may be unresponsive to the usual doses of epinephrine used to treat anaphylactic reactions.

5.6 Potentiation of Muscle Weakness

Beta-adrenergic blockade has been reported to potentiate muscle weakness consistent with certain myasthenic symptoms (e.g., diplopia, ptosis, and generalized weakness). Timolol has been reported rarely to increase muscle weakness in some patients with myasthenia gravis or myasthenic symptoms.

5.7 Masking of Hypoglycemic Symptoms in Patients with Diabetes Mellitus

Beta-adrenergic blocking agents should be administered with caution in patients subject to spontaneous hypoglycemia or to diabetic patients (especially those with labile diabetes) who are receiving insulin or oral hypoglycemic agents. Beta-adrenergic receptor blocking agents may mask the signs and symptoms of acute hypoglycemia.

5.8 Masking of Thyrotoxicosis

Beta-adrenergic blocking agents may mask certain clinical signs (e.g., tachycardia) of hyperthyroidism. Patients suspected of developing thyrotoxicosis should be managed carefully to avoid abrupt withdrawal of beta-adrenergic blocking agents that might precipitate a thyroid storm.

5.9 Renal and Hepatic Impairment

Dorzolamide has not been studied in patients with severe renal impairment (CrCl <30 mL/min). Because dorzolamide and its metabolite are excreted predominantly by the kidney, COSOPT is not recommended in such patients.

Dorzolamide has not been studied in patients with hepatic impairment and should therefore be used with caution in such patients.

5.10 Impairment of Beta-Adrenergically Mediated Reflexes During Surgery

The necessity or desirability of withdrawal of beta-adrenergic blocking agents prior to major surgery is controversial. Beta-adrenergic receptor blockade impairs the ability of the heart to respond to beta-adrenergically mediated reflex stimuli. This may augment the risk of general anesthesia in surgical procedures. Some patients receiving beta-adrenergic receptor blocking agents have experienced protracted severe hypotension during anesthesia. Difficulty in restarting and maintaining the heartbeat has also been reported. For these reasons, in patients undergoing elective surgery, some authorities recommend gradual withdraw of beta-adrenergic receptor blocking agents.

If necessary during surgery, the effects of beta-adrenergic blocking agents may be reversed by sufficient doses of adrenergic agonists.

5.11 Corneal Endothelium

Carbonic anhydrase activity has been observed in both the cytoplasm and around the plasma membranes of the corneal endothelium. There is an increased potential for developing corneal edema in patients with low endothelial cell counts. Caution should be used when prescribing COSOPT to this group of patients.

5.12 Bacterial Keratitis

There have been reports of bacterial keratitis associated with the use of multiple-dose containers of topical ophthalmic products. These containers had been inadvertently contaminated by patients who, in most cases, had a concurrent corneal disease or a disruption of the ocular epithelial.

6 ADVERSE REACTIONS

6.1 Clinical Trials Experience

Because clinical trials are conducted under widely varying conditions, adverse reaction rates observed in the clinical trials of a drug cannot be directly compared to rates in the clinical trials of another drug and may not reflect the rates observed in practice.

COSOPT was evaluated in 1,035 patients with elevated intraocular pressure treated for open-angle glaucoma or ocular hypertension for up to 15 months. Approximately 5% of all patients discontinued therapy because of adverse reactions.

The most frequently reported adverse reactions occurring in up to 30% of patients were taste perversion (bitter, sour, or unusual taste) or ocular burning and/or stinging. The following adverse reactions were reported in 5 to 15% of patients: conjunctival hyperemia, blurred vision, superficial punctate keratitis or eye itching.

The following adverse reactions were reported in 1 to 5% of patients: abdominal pain, back pain, blepharitis, bronchitis, cloudy vision, conjunctival discharge, conjunctival edema, conjunctival follicles, conjunctival injection, conjunctivitis, corneal erosion, corneal staining, cortical lens opacity, cough, dizziness, dryness of eyes, dyspepsia, eye debris, eye discharge, eye pain, eye tearing, eyelid edema, eyelid erythema, eyelid exudate/scales, eyelid pain or discomfort, foreign body sensation, glaucomatous cupping, headache, hypertension, influenza, lens nucleus coloration, lens opacity, nausea, nuclear lens opacity, pharyngitis, post-subcapsular cataract, sinusitis, upper respiratory infection, urinary tract infection, visual field defect, vitreous detachment.

Other adverse reactions that have been reported with the individual components are listed below:

Dorzolamide 2%

Angioedema, asthenia/fatigue, bronchospasm, contact dermatitis, epistaxis, eyelid crusting, ocular discomfort, photophobia, signs and symptoms of ocular allergic reaction, transient myopia.

Timolol (ocular administration)

Body as a Whole: Asthenia/fatigue; Cardiovascular: Arrhythmia, syncope, cerebral ischemia, worsening of angina pectoris, palpitation, cardiac arrest, pulmonary edema, edema, claudication, Raynaud's phenomenon, and cold hands and feet; Digestive: Anorexia, abdominal pain; Immunologic: Systemic lupus erythematosus; Nervous System/Psychiatric: Increase in signs and symptoms of myasthenia gravis, somnolence, insomnia, nightmares, behavioral changes and psychic disturbances including confusion, hallucinations, anxiety, disorientation, nervousness, and memory loss; Skin: Alopecia, psoriasiform rash or exacerbation of psoriasis; Hypersensitivity: Signs and symptoms of systemic allergic reactions, including anaphylaxis, angioedema, urticaria, and localized and generalized rash; Respiratory: Bronchospasm (predominantly in patients with pre-existing bronchospastic disease); Endocrine: Masked symptoms of hypoglycemia in diabetic patients; Special Senses: Ptosis, decreased corneal sensitivity, cystoid macular edema, visual disturbances including refractive changes and diplopia, pseudopemphigoid, and tinnitus; Urogenital: Retroperitoneal fibrosis, decreased libido, impotence, and Peyronie's disease; Musculoskeletal: Myalgia.

6.2 Postmarketing Experience

The following adverse reactions have been identified during post-approval use of COSOPT. Because these reactions are reported voluntarily from a population of uncertain size, it is not always possible to reliably estimate their frequency or establish a causal relationship to drug exposure: bradycardia, cardiac failure, cerebral vascular accident, chest pain, choroidal detachment following filtration surgery, depression, diarrhea, dry mouth, dyspnea, heart block, hypotension, iridocyclitis, myocardial infarction, nasal congestion, Stevens-Johnson syndrome, toxic epidermal necrolysis, paresthesia, photophobia, respiratory failure, skin rashes, urolithiasis, and vomiting.

Timolol (oral administration)

The following additional adverse reactions have been reported in clinical experience with ORAL timolol maleate or other ORAL beta-blocking agents and may be considered potential effects of ophthalmic timolol maleate: Allergic: Erythematous rash, fever combined with aching and sore throat, laryngospasm with respiratory distress; Body as a Whole: Extremity pain, decreased exercise tolerance, weight loss; Cardiovascular: Worsening of arterial insufficiency, vasodilatation; Digestive: Gastrointestinal pain, hepatomegaly, mesenteric arterial thrombosis, ischemic colitis; Hematologic: Nonthrombocytopenic purpura; thrombocytopenic purpura, agranulocytosis; Endocrine: Hyperglycemia, hypoglycemia; Skin: Pruritus, skin irritation, increased pigmentation, sweating; Musculoskeletal: Arthralgia; Nervous System/Psychiatric: Vertigo, local weakness, diminished concentration, reversible mental depression progressing to catatonia, an acute reversible syndrome characterized by disorientation for time and place, emotional lability, slightly clouded sensorium, and deceased performance on neuropsychometrics; Respiratory: Rales, bronchial obstruction; Urogenital: Urination difficulties.

7 DRUG INTERACTIONS

7.1 Oral Carbonic Anhydrase Inhibitors

There is a potential for an additive effect on the known systemic effects of carbonic anhydrase inhibition in patients receiving an oral carbonic anhydrase inhibitor and COSOPT. The concomitant administration of COSOPT and oral carbonic anhydrase inhibitors is not recommended.

7.2 High-Dose Salicylate Therapy

Although acid-base and electrolyte disturbances were not reported in the clinical trials with dorzolamide hydrochloride ophthalmic solution, these disturbances have been reported with oral carbonic anhydrase inhibitors and have, in some instances, resulted in drug interactions (e.g., toxicity associated with high-dose salicylate therapy). Therefore, the potential for such drug interactions should be considered in patients receiving COSOPT.

7.3 Beta-Adrenergic Blocking Agents

Patients who are receiving a beta-adrenergic blocking agent orally and COSOPT should be observed for potential additive effects of beta-blockade, both systemic and on intraocular pressure. The concomitant use of two topical beta-adrenergic blocking agents is not recommended.

7.4 Calcium Antagonists

Caution should be used in the coadministration of beta-adrenergic blocking agents, such as COSOPT, and oral or intravenous calcium antagonists because of possible atrioventricular conduction disturbances, left ventricular failure, and hypotension. In patients with impaired cardiac function, coadministration should be avoided.

7.5 Catecholamine-Depleting Drugs

Close observation of the patient is recommended when a beta-blocker is administered to patients receiving catecholamine-depleting drugs, such as reserpine, because of possible additive effects and the production of hypotension and/or marked bradycardia, which may result in vertigo, syncope, or postural hypotension.

7.6 Digitalis and Calcium Antagonists

The concomitant use of beta-adrenergic blocking agents with digitalis and calcium antagonists may have additive effects in prolonging atrioventricular conduction time.

7.7 CYP2D6 Inhibitors

Potentiated systemic beta-blockade (e.g., decreased heart rate, depression) has been reported during combined treatment with CYP2D6 inhibitors (e.g., quinidine, SSRIs) and timolol.

7.8 Clonidine

Oral beta-adrenergic blocking agents may exacerbate the rebound hypertension which can follow the withdrawal of clonidine. There have been no reports of exacerbation of rebound hypertension with ophthalmic timolol maleate.

8 USE IN SPECIFIC POPULATIONS

8.1 Pregnancy

TERATOGENIC EFFECTS

Teratogenic Effects. Developmental toxicity studies with dorzolamide hydrochloride in rabbits at oral doses of ≥2.5 mg/kg/day (37 times the recommended human ophthalmic dose) revealed malformations of the vertebral bodies. These malformations occurred at doses that caused metabolic acidosis with decreased body weight gain in dams and decreased fetal weights. No treatment-related malformations were seen at 1 mg/kg/day (15 times the recommended human ophthalmic dose).

Teratogenicity studies with timolol in mice, rats, and rabbits at oral doses up to 50 mg/kg/day (7,000 times the systemic exposure following the maximum recommended human ophthalmic dose) demonstrated no evidence of fetal malformations. Although delayed fetal ossification was observed at this dose in rats, there were no adverse effects on postnatal development of offspring. Doses of 1,000 mg/kg/day (142,000 times the systemic exposure following the maximum recommended human ophthalmic dose) were maternotoxic in mice and resulted in an increased number of fetal resorptions. Increased fetal resorptions were also seen in rabbits at doses of 14,000 times the systemic exposure following the maximum recommended human ophthalmic dose, in this case without apparent maternotoxicity.

There are no adequate and well-controlled studies in pregnant women. COSOPT should be used during pregnancy only if the potential benefit justifies the potential risk to the fetus.

8.3 Nursing Mothers

It is not known whether dorzolamide is excreted in human milk. Timolol maleate has been detected in human milk following oral and ophthalmic drug administration. Because of the potential for serious adverse reactions from COSOPT in nursing infants, a decision should be made whether to discontinue nursing or to discontinue the drug, taking into account the importance of the drug to the mother.

8.4 Pediatric Use

The safety and effectiveness of dorzolamide hydrochloride ophthalmic solution and timolol maleate ophthalmic solution have been established when administered individually in pediatric patients aged 2 years and older. Use of these drug products in these children is supported by evidence from adequate and well-controlled studies in children and adults. Safety and efficacy in pediatric patients below the age of 2 years have not be established.

8.5 Geriatric Use

No overall differences in safety or effectiveness have been observed between elderly and younger patients.

10 OVERDOSAGE

Symptoms consistent with systemic administration of beta-blockers or carbonic anhydrase inhibitors may occur, including electrolyte imbalance, development of an acidotic state, dizziness, headache, shortness of breath, bradycardia, bronchospasm, cardiac arrest and possible central nervous system effects. Serum electrolyte levels (particularly potassium) and blood pH levels should be monitored. [see Adverse Reactions (6)] .

A study of patients with renal failure showed that timolol did not dialyze readily.

11 DESCRIPTION

COSOPT (dorzolamide hydrochloride and timolol maleate ophthalmic solution) is the combination of a topical carbonic anhydrase inhibitor and a topical beta-adrenergic receptor blocking agent.

Dorzolamide hydrochloride is described chemically as: (4 S-trans)-4-(ethylamino)-5,6-dihydro-6-methyl-4 H-thieno[2,3- b]thiopyran-2-sulfonamide 7,7-dioxide monohydrochloride. Dorzolamide hydrochloride is optically active. The specific rotation is:

 | [α] | 25°C | (C=1, water) = ~-17°.
 |  | 405 nm

Its empirical formula is C10H16N2O4S3 ∙ HCl and its structural formula is:

Dorzolamide hydrochloride has a molecular weight of 360.91. It is a white to off-white, crystalline powder, which is soluble in water and slightly soluble in methanol and ethanol.

Timolol maleate is described chemically as: (-)-1-(tert-butylamino)-3-[(4-morpholino-1,2,5-thiadiazol-3-yl)oxy]-2-propanol maleate (1:1) (salt). Timolol maleate possesses an asymmetric carbon atom in its structure and is provided as the levo-isomer. The optical rotation of timolol maleate is:

 | [α] | 25°C | in 1N HCl (C = 5) = -12.2° (-11.7° to -12.5°).
 |  | 405 nm

Its molecular formula is C13H24N4O3S ∙ C4H4O4 and its structural formula is:

Timolol maleate has a molecular weight of 432.50. It is a white, odorless, crystalline powder which is soluble in water, methanol, and alcohol. Timolol maleate is stable at room temperature.

COSOPT is supplied as a sterile, clear, colorless to nearly colorless, isotonic, buffered, slightly viscous, aqueous solution. The pH of the solution is approximately 5.65, and the osmolarity is 242 to 323 mOsM. Each mL of COSOPT contains 20 mg dorzolamide (equivalent to 22.26 mg of dorzolamide hydrochloride) and 5 mg timolol (equivalent to 6.83 mg timolol maleate). Inactive ingredients are sodium citrate, hydroxyethyl cellulose, sodium hydroxide, mannitol, and water for injection. Benzalkonium chloride 0.0075% is added as a preservative.

12 CLINICAL PHARMACOLOGY

12.1 Mechanism of Action

COSOPT is comprised of two components: dorzolamide hydrochloride and timolol maleate. Each of these two components decreases elevated intraocular pressure, whether or not associated with glaucoma, by reducing aqueous humor secretion. Elevated intraocular pressure is a major risk factor in the pathogenesis of optic nerve damage and glaucomatous visual field loss. The higher the level of intraocular pressure, the greater the likelihood of glaucomatous field loss and optic nerve damage.

Dorzolamide hydrochloride is an inhibitor of human carbonic anhydrase II. Inhibition of carbonic anhydrase in the ciliary processes of the eye decreases aqueous humor secretion, presumably by slowing the formation of bicarbonate ions with subsequent reduction in sodium and fluid transport. Timolol maleate is a beta1 and beta2 (non-selective) adrenergic receptor blocking agent that does not have significant intrinsic sympathomimetic, direct myocardial depressant, or local anesthetic (membrane-stabilizing) activity. The combined effect of these two agents administered as COSOPT twice daily results in additional intraocular pressure reduction compared to either component administered alone, but the reduction is not as much as when dorzolamide administered three times daily and timolol twice daily are administered concomitantly. [see Clinical Studies (14)] .

12.3 Pharmacokinetics

Dorzolamide Hydrochloride

When topically applied, dorzolamide reaches the systemic circulation. To assess the potential for systemic carbonic anhydrase inhibition following topical administration, drug and metabolite concentrations in RBCs and plasma and carbonic anhydrase inhibition in RBCs were measured. Dorzolamide accumulates in RBCs during chronic dosing as a result of binding to CA-II. The parent drug forms a single N-desethyl metabolite, which inhibits CA-II less potently than the parent drug but also inhibits CA-I. The metabolite also accumulates in RBCs where it binds primarily to CA-I. Plasma concentrations of dorzolamide and metabolite are generally below the assay limit of quantitation (15nM). Dorzolamide binds moderately to plasma proteins (approximately 33%).

Dorzolamide is primarily excreted unchanged in the urine; the metabolite also is excreted in urine. After dosing is stopped, dorzolamide washes out of RBCs nonlinearly, resulting in a rapid decline of drug concentration initially, followed by a slower elimination phase with a half-life of about four months.

To simulate the systemic exposure after long-term topical ocular administration, dorzolamide was given orally to eight healthy subjects for up to 20 weeks. The oral dose of 2 mg twice daily closely approximates the amount of drug delivered by topical ocular administration of dorzolamide 2% three times daily. Steady state was reached within 8 weeks. The inhibition of CA-II and total carbonic anhydrase activities was below the degree of inhibition anticipated to be necessary for a pharmacological effect on renal function and respiration in healthy individuals.

Timolol Maleate

In a study of plasma drug concentrations in six subjects, the systemic exposure to timolol was determined following twice daily topical administration of timolol maleate ophthalmic solution 0.5%. The mean peak plasma concentration following morning dosing was 0.46 ng/mL.

13 NONCLINICAL TOXICOLOGY

13.1 Carcinogenesis, Mutagenesis, Impairment of Fertility

In a two-year study of dorzolamide hydrochloride administered orally to male and female Sprague-Dawley rats, urinary bladder papillomas were seen in male rats in the highest dosage group of 20 mg/kg/day (250 times the recommended human ophthalmic dose). Papillomas were not seen in rats given oral doses equivalent to approximately 12 times the recommended human ophthalmic dose. No treatment-related tumors were seen in a 21-month study in female and male mice given oral doses up to 75 mg/kg/day (~900 times the recommended human ophthalmic dose). The increased incidence of urinary bladder papillomas seen in the high-dose male rats is a class-effect of carbonic anhydrase inhibitors in rats. Rats are particularly prone to developing papillomas in response to foreign bodies, compounds causing crystalluria, and diverse sodium salts.

No changes in bladder urothelium were seen in dogs given oral dorzolamide hydrochloride for one year at 2 mg/kg/day (25 times the recommended human ophthalmic dose) or monkeys dosed topically to the eye at 0.4 mg/kg/day (~5 times the recommended human ophthalmic dose) for one year.

In a two-year study of timolol maleate administered orally to rats, there was a statistically significant increase in the incidence of adrenal pheochromocytomas in male rats administered 300 mg/kg/day (approximately 42,000 times the systemic exposure following the maximum recommended human ophthalmic dose). Similar differences were not observed in rats administered oral doses equivalent to approximately 14,000 times the maximum recommended human ophthalmic dose.

In a lifetime oral study of timolol maleate in mice, there were statistically significant increases in the incidence of benign and malignant pulmonary tumors, benign uterine polyps and mammary adenocarcinomas in female mice at 500 mg/kg/day, (approximately 71,000 times the systemic exposure following the maximum recommended human ophthalmic dose), but not at 5 or 50 mg/kg/day (approximately 700 or 7,000, respectively, times the systemic exposure following the maximum recommended human ophthalmic dose). In a subsequent study in female mice, in which post-mortem examinations were limited to the uterus and the lungs, a statistically significant increase in the incidence of pulmonary tumors was again observed at 500 mg/kg/day.

The increased occurrence of mammary adenocarcinomas was associated with elevations in serum prolactin which occurred in female mice administered oral timolol at 500 mg/kg/day, but not at doses of 5 or 50 mg/kg/day. An increased incidence of mammary adenocarcinomas in rodents has been associated with administration of several other therapeutic agents that elevate serum prolactin, but no correlation between serum prolactin levels and mammary tumors has been established in humans. Furthermore, in adult human female subjects who received oral dosages of up to 60 mg of timolol maleate (the maximum recommended human oral dosage), there were no clinically meaningful changes in serum prolactin.

The following tests for mutagenic potential were negative for dorzolamide: (1) in vivo (mouse) cytogenetic assay; (2) in vitro chromosomal aberration assay; (3) alkaline elution assay; (4) V-79 assay; and (5) Ames test.

Timolol maleate was devoid of mutagenic potential when tested in vivo (mouse) in the micronucleus test and cytogenetic assay (doses up to 800 mg/kg) and in vitro in a neoplastic cell transformation assay (up to 100 mcg/mL). In Ames tests the highest concentrations of timolol employed, 5,000 or 10,000 mcg/plate, were associated with statistically significant elevations of revertants observed with tester strain TA100 (in seven replicate assays), but not in the remaining three strains. In the assays with tester strain TA100, no consistent dose response relationship was observed, and the ratio of test to control revertants did not reach 2. A ratio of 2 is usually considered the criterion for a positive Ames test.

Reproduction and fertility studies in rats with either timolol maleate or dorzolamide hydrochloride demonstrated no adverse effect on male or female fertility at doses up to approximately 100 times the systemic exposure following the maximum recommended human ophthalmic dose.

14 CLINICAL STUDIES

Clinical studies of 3 to 15 months duration were conducted to compare the IOP-lowering effect over the course of the day COSOPT twice daily (dosed morning and bedtime) to individually and concomitantly administered 0.5% timolol twice daily and 2% dorzolamide twice and three times daily. The IOP-lowering effect of COSOPT twice daily was greater (1 to 3 mmHg) than that of monotherapy with either 2% dorzolamide three times daily or 0.5% timolol twice daily. The IOP-lowering effect of COSOPT twice daily was approximately 1 mmHg less than that of concomitant therapy with 2% dorzolamide three times daily and 0.5% timolol twice daily.

Open-label extensions of two studies were conducted for up to 12 months. During this period, the IOP-lowering effect of COSOPT twice daily was consistent during the 12 month follow-up period.

16 HOW SUPPLIED/STORAGE AND HANDLING

COSOPT® (dorzolamide hydrochloride and timolol maleate ophthalmic solution) 2% / 0.5% is supplied in 10 mL white low-density polyethylene (LDPE) plastic bottles with white LDPE dropper tips and blue P/P as follows:

NDC 82584-605-10 10 mL capacity bottle.

STORAGE AND HANDLING

Storage: Store at 20° to 25°C (68° to 77°F). Protect from light. After opening, COSOPT can be used until the expiration date on the bottle.

17 PATIENT COUNSELING INFORMATION

Advise the patient to read the FDA-Approved patient labeling (Patient Information and Instructions for Use).

Potential for Exacerbation of Asthma and COPD

COSOPT may cause severe worsening of asthma and COPD symptoms including death due to bronchospasm. Advise patients with bronchial asthma, a history of bronchial asthma, or severe chronic obstructive pulmonary disease not to take this product. [see Contraindications (4.1)] .

Potential of Cardiovascular Effects

COSOPT may cause worsening of cardiac symptoms. Advise patients with sinus bradycardia, second or third degree atrioventricular block, or cardiac failure not to take this product. [see Contraindications (4.2)] .

Sulfonamide Reactions

COSOPT contains dorzolamide (which is a sulfonamide) and, although administered topically, is absorbed systemically. Therefore the same types of adverse reactions that are attributable to sulfonamides may occur with topical administration, including severe skin reactions. Advise patients that if serious or unusual reactions or signs of hypersensitivity occur, they should discontinue the use of the product and seek their physician's advise. [see Warnings and Precautions (5.3)] .

Handling Ophthalmic Solutions

Instruct patients that ocular solutions, if handled improperly or if the tip of the dispensing container contacts the eye or surrounding structures, can be contaminated by common bacteria known to cause ocular infections. Serious damage to the eye and subsequent loss of vision may result from using contaminated solutions [see Warnings and Precautions (5.12)] .

Intercurrent Ocular Conditions

Advise patients that if they have ocular surgery or develop an intercurrent ocular condition (e.g., trauma or infection), they should immediately seek their physician's advice concerning the continued use of the present multidose container.

Concomitant Topical Ocular Therapy

If more than one topical ophthalmic drug is being used, the drugs should be administered at least five minutes apart.

Contact Lens Use

Advise patients that COSOPT contains benzalkonium chloride which may be absorbed by soft contact lenses. Contact lenses should be removed prior to administration of the solution. Lenses may be reinserted 15 minutes following administration of COSOPT.

Manufactured for: Thea Pharm Inc. Waltham, MA 02451
Made in Switzerland

© 2023. Thea Pharma Inc. All rights reserved
The COSOPT trademarks are owned by
Merck Sharp & Dohme Corp. and are being used with permission.
Rev. 05/2023

PATIENT INFORMATION COSOPT® (CO-sopt) (dorzolamide hydrochloride and timolol maleate ophthalmic solution) for topical ophthalmic use

What is COSOPT?

COSOPT is a prescription eye drop solution that contains two medicines, dorzolamide hydrochloride called an ophthalmic carbonic anhydrase and timolol maleate called a beta-blocker.

COSOPT is used to lower high pressure in the eye in people with open-angle glaucoma or ocular hypertension when a beta-blocking medicine alone does not work to control the eye pressure. It is not known if COSOPT is safe and effective in children 2 years of age and younger.

Do not use COSOPT if you:

- have or have had asthma.
- have chronic obstructive pulmonary disease (COPD) which emphysema, chronic bronchitis or both.
- have heart problems including a slow heartbeat, heart block, heart failure, or your heart muscle suddenly becomes weak due to a severe heart attack or other heart problem that caused heart damage (cardiogenic shock).
- are allergic to any of the ingredients in COSOPT. See the end of this Patient Information leaflet for a complete list of ingredients in COSOPT.

Before using COSOPT, tell your healthcare provider about all your medical conditions, including if you:

- have or have had allergies to sulfa drugs
- have a history of anaphylactic reactions to allergens
- have atopy (genetic disposition to develop allergic reactions)
- have or have had muscle weakness or myasthenia gravis
- have diabetes
- have thyroid disease
- have or have had kidney or liver problems
- plan to have any type of surgery
- wear contact lenses
- are using any other eye drops
- have an eye infection or eye trauma
- are pregnant or plan to become pregnant. It is not know if COSOPT will harm your unborn baby. Tell your healthcare provider right away if you become pregnant while using COSOPT. You and your healthcare provider will decide if you should use COSOPT while you are pregnant.
- are breastfeeding or plan to breastfeed. It is not known if COSOPT passes into breastmilk. Talk to your healthcare provider about the best way to feed your baby while using COSOPT.

Tell your healthcare provider about all the medicines you take, including prescription and over-the-counter medicines, vitamins, and herbal supplements.

COSOPT may affect the way medicines work, and other medicines may affect how COSOPT works. Do not start a new medicine without first talking to your healthcare provider.

Ask your healthcare provider or pharmacist for a list of medicines you are using, if you are not sure. Know the medicines you take. Keep a list of them and show it to your healthcare provider and pharmacist when you get a new medicine.

How should I use COSOPT?

- See the complete Instructions for Use at the end of this Patient Information leaflet for detailed instructions about the right way to use COSOPT.
- Use COSOPT exactly as your healthcare provider tells you.
- Use 1 drop of COSOPT in the affected eye or both eyes if needed, 2 times each day. 1 drop in the morning and 1 drop in the evening.
- If you are using COSOPT with another eyedrop, wait at least 5 minutes before or after using COSOPT.
- If you have eye surgery or have any problems with your eye such as trauma or an infection, talk to your healthcare provider about continuing to use the bottle (multidose) that contains COSOPT.
- COSOPT contains a preservative called benzalkonium chloride. The preservative may be absorbed by soft contact lenses. If you wear contact lenses, remove them before using COSOPT. The lenses can be placed back into your eyes 15 minutes after using COSOPT.
- Do not touch your eye or eyelid with the dropper tip. Eye medicines, not handled the right way, can become contaminated by bacteria that can cause eye infections. Serious damage to the eye and followed by loss of vision may happen from using contaminated eye medicines. If you think your COSOPT medicine may be contaminated, or if you develop an eye infection, contact your healthcare provider right away about continuing to use your bottle of COSOPT.
- If you use too much COSOPT you may have dizziness, headaches, shortness of breath, slow heartbeats, or problems breathing. If you have any of these symptoms call your healthcare provider or go to the nearest hospital emergency room right away.

What are the possible side effects of COSOPT?

COSOPT may cause serious side effects, including:

- severe breathing problems. These breathing problems can happen in people who have asthma, chronic obstructive pulmonary disease, or heart failure and can cause death. Tell your healthcare provider right away if you have breathing problems while using COSOPT.
- heart failure. This can happen in people who already have heart failure and in people who have never had heart failure before. Tell your healthcare provider right away if you get any of these symptoms of heart failure while taking COSOPT:
  - shortness of breath
  - irregular heartbeat (palpitations)
  - swelling of your ankles or feet
  - sudden weight gain
- serious sulfa (sulfonamide) reactions. Serious reactions including death can happen in people who are allergic to sulfonamide medicines like one of the medicines in COSOPT. Other serious reactions can include:
  - severe skin reactions
  - liver problems
  - blood problems
  Stop using COSOPT and call your healthcare provider or get emergency help right away if you get any of these symptoms of an allergic reaction:
  - swelling of your face, lips, mouth, or tongue
  - trouble breathing
  - wheezing
  - severe itching
  - skin rash, redness, or swelling
  - dizziness or fainting
  - fast heartbeat or pounding in your chest
  - sweating
- increased allergic reactions. People who have a genetic history of developing allergies (atopy) or who have a history of severe anaphylactic reactions from different allergens may have increased allergic reactions while taking beta-blockers, like one of the medicines in COSOPT. Your usual dose of epinephrine used to treat your anaphylactic reactions may not work as well. Stop using COSOPT and call your healthcare provider or get emergency help right away if you get any of these symptoms of an allergic reaction:
  - swelling of your face, lips, mouth or tongue
  - trouble breathing
  - wheezing
  - severe itching
  - skin rash, redness, or swelling
  - dizziness or fainting
  - fast heartbeat or pounding in your chest
  - sweating
- worsening muscle weakness. Muscle weakness symptoms including double vision or drooping eyelids can happen while using COSOPT. Muscle weakness can get worse in people who already have problems with muscle weakness like myasthenia gravis.
- swelling of eye. Some people with low counts of certain types of cells in the eye have developed corneal edema when using COSOPT. Call your healthcare provider if you have swelling in your eyes.

The most common side effects of COSOPT include:

- eye burning
- eye stinging
- eye redness
- blurred vision
- eye tearing
- eye itching
- a bitter, sour, or unusual taste after putting in your eyedrops

These are not all the possible side effects of COSOPT.

Call your doctor for medical advice about side effects. You may report side effects to FDA at 1-800-FDA-1088.

How should I store COSOPT?

- Store at 68° to 77°F (20° to 25°C).
- Protect from light.
- Do not use COSOPT after the expiration date on the bottle.

Keep COSOPT and all medicines out of the reach of children.

General information about the safe and effective use of COSOPT.

Medicines are sometimes prescribed for purposes other than those listed in a Patient Information leaflet. Do not use COSOPT for a condition for which it was not prescribed. Do not give COSOPT to other people, even if they have the same symptoms that you have. It may harm them.

You can ask your pharmacist or healthcare provider for information about COSOPT that is written for health professionals.

What are the ingredients in COSOPT?

Active ingredients: dorzolamide hydrochloride and timolol maleate

Inactive ingredients: sodium citrate, hydroxyethyl cellulose, sodium hydroxide, mannitol, water for injection and benzalkonium chloride added as a preservative.

This Patient Package Information has been approved by the U.S. Food and Drug Administration | 11/2020

INSTRUCTIONS FOR USE COSOPT® (CO-sopt) (dorzolamide hydrochloride and timolol maleate ophthalmic solution) for topical ophthalmic use

Read this Instructions for Use before you start using COSOPT and each time you get a refill. There may be new information. This leaflet does not take the place of talking to your healthcare provider about your medical condition or treatment.

Important Information:

- COSOPT is for use in the eye.
- If you are using COSOPT with another eyedrop, wait at least 5 minutes before or after using COSOPT.
- If you wear contact lenses, remove them before using COSOPT. The lenses can be placed back into your eyes 15 minutes after using COSOPT.
- Do not touch your eye or eyelid with the dropper tip. Eye medicines, not handled the right way, can become contaminated by bacteria that can cause eye infections. Serious damage to the eye and followed by loss of vision may happen from using contaminated eye medicines. If you think your COSOPT medicine may be contaminated, or if you develop an eye infection, contact your healthcare provider right away about continuing to use your bottle of COSOPT.
- Wash your hands before each use to make sure you do not infect your eyes while using COSOPT.
- Before using the eyedrops for the first time, be sure the Safety Seal around the cap is not broken. If the Safety Seal is broken, call your pharmacist to get a new bottle of COSOPT.

 | Step 1. | Tear off the Safety Seal.
 | Step 2. | To open the COSOPT bottle, unscrew the cap by turning counterclockwise.
 | Step 3. | Tilt your head back. Gently pull your lower eyelid downwards to form a pocket between your eyelid and your eye, look up (See Figure A).
 | Step 4. | Turn the COSOPT bottle upside down.
 | Step 5. | Place the dropper tip of the COSOPT bottle close to your eye but be careful not to touch your eye with it. Gently press the COSOPT bottle lightly with your thumb or index finger until 1 drop of COSOPT falls into your eye (See Figure B).
 | Step 6. | Repeat Steps 4 and 5 with the other eye if instructed to do so by your healthcare provider.
 | Step 7. | Replace the cap by turning until it is firmly touching the bottle. Do not overtighten the cap.
 | Step 8. | If you use contact lenses, wait at least 15 minutes before placing them back into your eyes.

- The dropper tip is made to give a single drop of COSOPT. Do not enlarge the hole of the dropper tip.
- After you have used all of your doses of COSOPT, there will be some COSOPT left in the bottle.
- There is an extra amount of COSOPT that has been added to the bottle. You will get the full amount of COSOPT that your doctor prescribed.
- Do not try to remove the extra COSOPT medicine from the bottle.

This Instructions for Use has been approved by the U.S. Food and Drug Administration | 11/2020

Manufactured for: Thea Pharma Inc. Waltham, MA 02451
Made in Switzerland

© 2023. Thea Pharma Inc. All rights reserved
The COSOPT trademarks are owned by Merck Sharp & Dohme Corp. and are being used with permission.

Rev. 05/2023

Revised: 5/2023

Thea Pharma Inc.

PRINCIPAL DISPLAY PANEL - 10 mL Bottle Carton

NDC 82584-605-10

Théa

10 mL

STERILE
OPHTHALMIC SOLUTION

COSOPT®
(dorzolamide
hydrochloride and
timolol maleate
ophthalmic solution)
2% / 0.5%

(dorzolamide hydrochloride
22.3 mg/mL and
timolol maleate 6.8 mg/mL)

Rx only